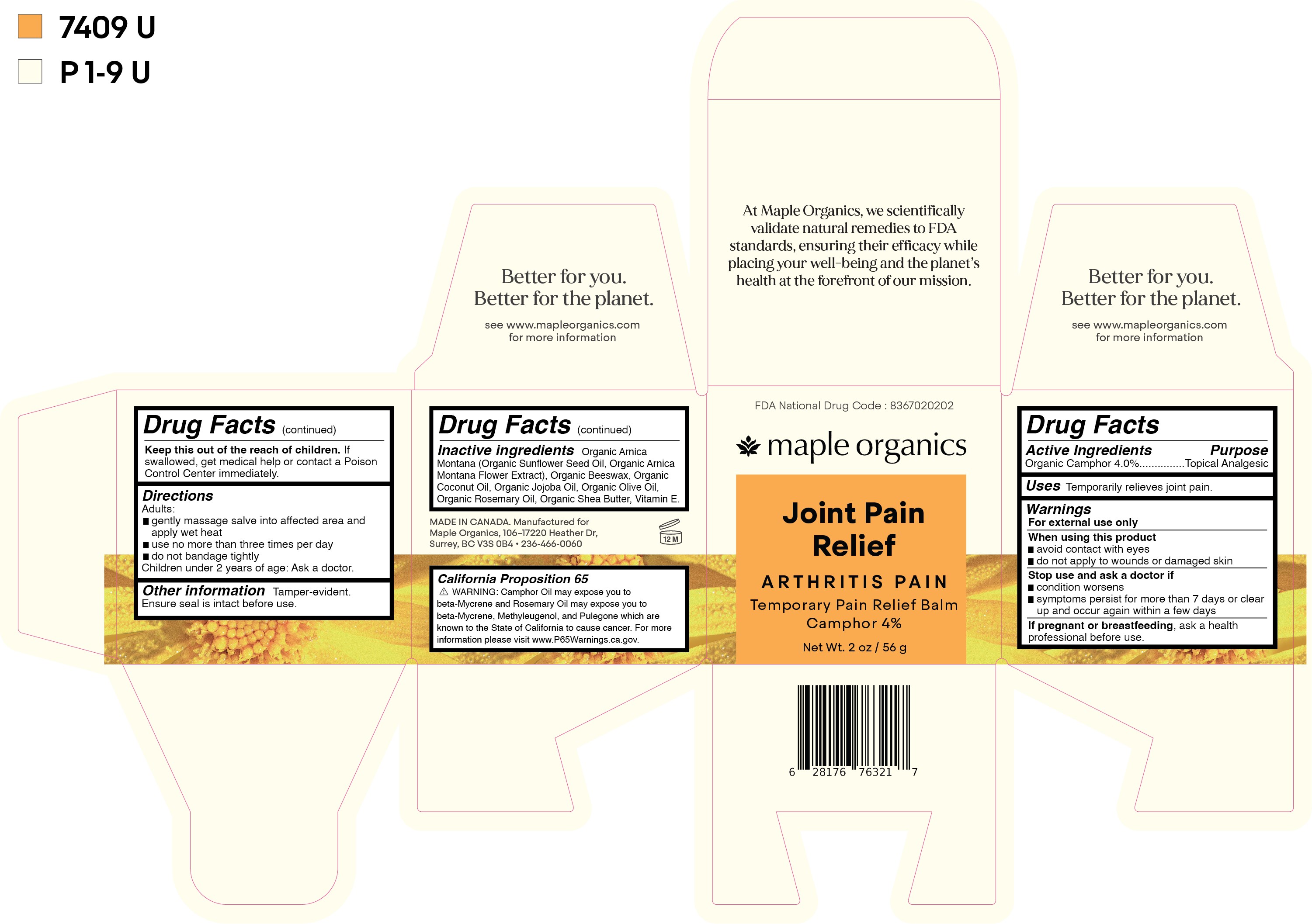 DRUG LABEL: Joint Therapy
NDC: 83670-202 | Form: SALVE
Manufacturer: Everlaan Organics Inc
Category: otc | Type: HUMAN OTC DRUG LABEL
Date: 20250127

ACTIVE INGREDIENTS: CAMPHOR (NATURAL) 4 g/100 g
INACTIVE INGREDIENTS: ROSEMARY OIL; .ALPHA.-TOCOPHEROL; ARNICA MONTANA; JOJOBA OIL; SUNFLOWER OIL; YELLOW WAX; COCONUT OIL; SHEA BUTTER; OLIVE OIL

Joint Pain Relief

Active ingredients

Organic Camphor 4.0%

Purpose

Organic Camphor 4.0%..............Topical Analgesic

Uses

Temporarily relieves joint pain.

Warnings

For external use only

When using this product

- avoid contact with eyes
- do not apply to wounds or damaged skin

Stop use and ask a doctor if

- condition worsens
- symptoms persist for more than 7 days or clear up and occur again within a few days

PREGNANCY OR BREAST FEEDING

If pregnant or breastfeeding, ask a health professional before use.

KEEP OUT OF REACH OF CHILDREN

Keep this out of the reach of children. If swallowed, get medical help or contact a Poison Control Center immediately.

Directions

Adults:

- gently massage salve into affected area and apply wet heat
- use no more than three times per day

Children under 2 years of age: Ask a doctor.

Other information

Tamper-evident. Ensure seal is intact before use.

Inactive ingredients

Organic Arnica Montana (Organic Sunflower Seed Oil, Organic Arnica Montana Flower Extract), Organic Beeswax, Organic Coconut Oil, Organic Jojoba Oil, Organic Olive Oil, Organic Rosemary Oil, Organic Shea Butter, Vitamin E

PACKAGE LABEL

maple organics

Joint Pain Relief

Arthritis Pain

Temporary Pain Relief Balm

Camphor 4%

Net Wt. 2 oz / 56 g